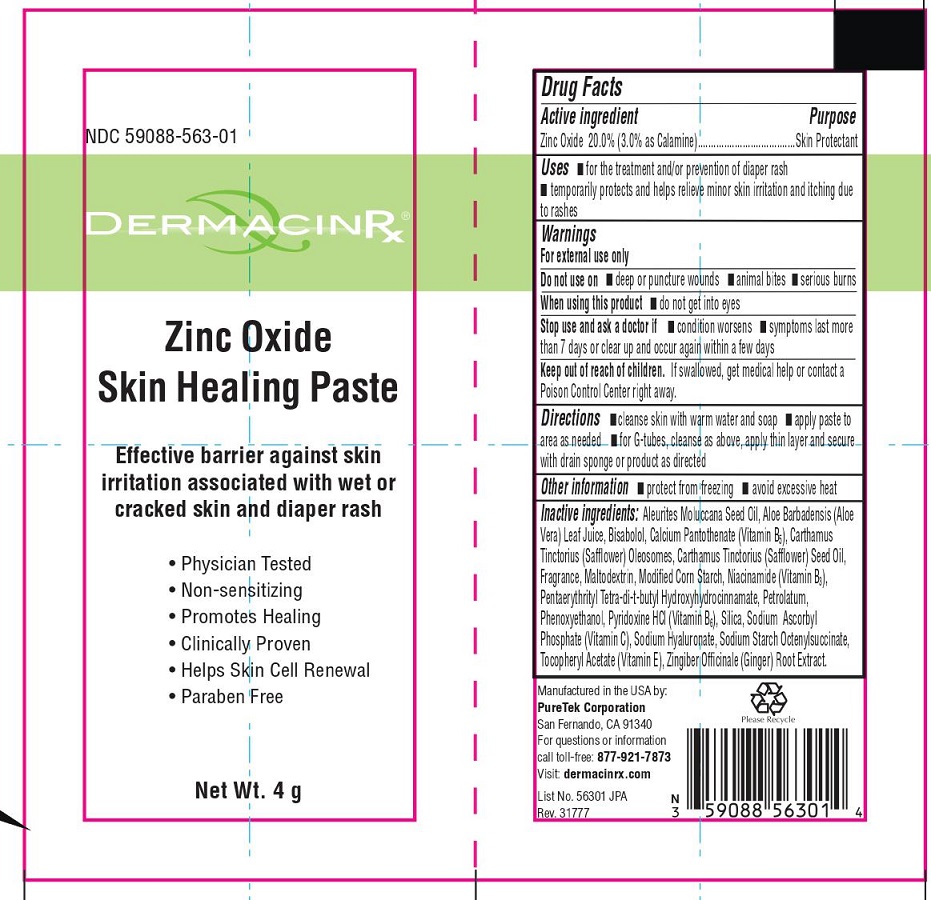 DRUG LABEL: DermacinRx Zinc Oxide Skin Healing
NDC: 59088-563 | Form: PASTE
Manufacturer: PureTek Corporation
Category: otc | Type: HUMAN OTC DRUG LABEL
Date: 20241002

ACTIVE INGREDIENTS: ZINC OXIDE 200 mg/1 g
INACTIVE INGREDIENTS: KUKUI NUT OIL; ALOE VERA LEAF; .ALPHA.-BISABOLOL, (+/-)-; CALCIUM PANTOTHENATE; CARTHAMUS TINCTORIUS (SAFFLOWER) OLEOSOMES; SAFFLOWER OIL; MALTODEXTRIN; MODIFIED CORN STARCH (1-OCTENYL SUCCINIC ANHYDRIDE); NIACINAMIDE; PENTAERYTHRITOL TETRAKIS(3-(3,5-DI-TERT-BUTYL-4-HYDROXYPHENYL)PROPIONATE); PETROLATUM; PHENOXYETHANOL; PYRIDOXINE HYDROCHLORIDE; SILICON DIOXIDE; SODIUM ASCORBYL PHOSPHATE; HYALURONATE SODIUM; .ALPHA.-TOCOPHEROL ACETATE; GINGER OIL

DermacinRx Zinc Oxide Skin Healing Paste
(Zinc Oxide)

Active ingredient

Zinc Oxide 20.0%

(3.0% as Calamine)

Purpose

Skin Protectant

Uses

- for the treatment and/or prevention of diaper rash
- temporarily protects and helps relieve minor skin irritation and itching due to rashes

Warnings

For external use only

Do not use on

- deep or puncture wounds
- animal bites
- serious burns

When using this product

- do not get into eyes

Stop use and ask a doctor if

- condition worsens
- symptoms last more than 7 days or clear up and occur again within a few days

Keep out of reach of childern.

If swallowed, get medical help or contact a Poison Control Center right away.

Directions

- cleanse skin with warm water and soap
- apply paste to area as needed
- for G-tubes, cleanse as above, apply thin layer and secure with drain sponge or product as directed

Other information

- protect from freezing
- avoid excessive heat

Inactive ingredients:

Aleurites Moluccana Seed Oil, Aloe Barbadensis (Aloe Vera) Leaf Juice, Bisabolol, Calcium Pantothenate (Vitamin B5), Carthamus Tinctorius (Safflower) Oleosomes, Carthamus Tinctorius (Safflower) Seed Oil, Fragrance, Maltodextrin, Modified Corn Starch, Niacinamide (Vitamin B3), Pentaerythrityl Tetra-di-t-butyl Hydroxyhydrocinnamate, Petrolatum, Phenoxyethanol, Pyridoxine HCl (Vitamin B6), Silica, Sodium Ascorbyl Phosphate (Vitamin C), Sodium Hyaluronate, Sodium Starch Octenylsuccinate, Tocopheryl Acetate (Vitamin E), Zingiber Officinale (Ginger) Root Extract.